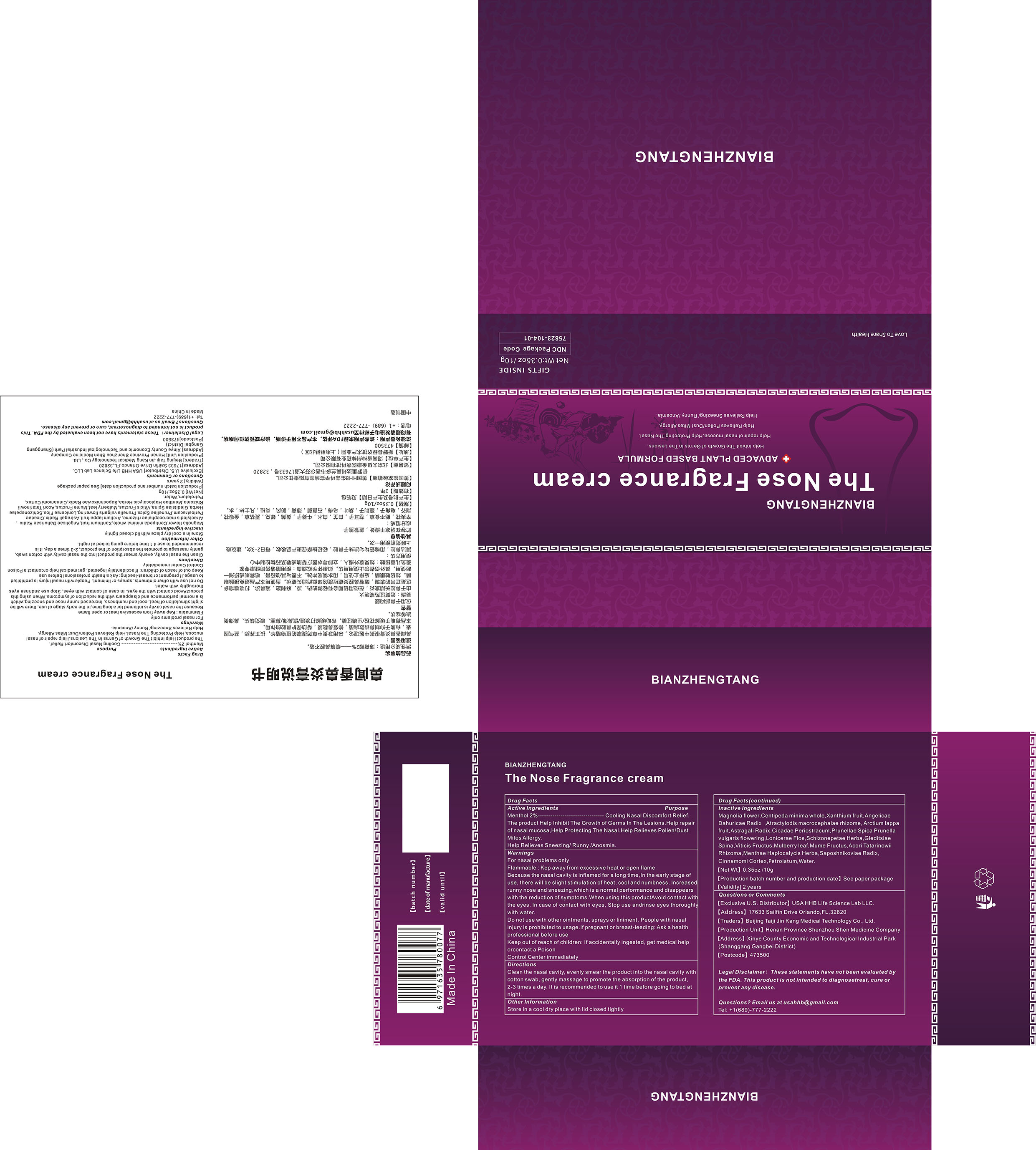 DRUG LABEL: The Nose Fragrance cream
NDC: 75823-104 | Form: CREAM
Manufacturer: Beijing Taiji Jin Kang Medical Technology Co., Ltd.
Category: otc | Type: HUMAN OTC DRUG LABEL
Date: 20200820

ACTIVE INGREDIENTS: MENTHOL 2 g/100 g
INACTIVE INGREDIENTS: VITEX ROTUNDIFOLIA FRUIT; MAGNOLIA SPRENGERI FLOWER BUD; CENTIPEDA MINIMA WHOLE; XANTHIUM SIBIRICUM FRUIT; ANGELICA DAHURICA ROOT; ATRACTYLODES MACROCEPHALA ROOT; PETROLATUM; ASTRAGALUS PROPINQUUS ROOT; CICADA PERIOSTRACUM; PRUNELLA VULGARIS FLOWERING TOP; LONICERA CONFUSA FLOWER; SCHIZONEPETA TENUFOLIA SPIKE; GLEDITSIA SINENSIS THORN; ARCTIUM LAPPA FRUIT; PRUNUS MUME FRUIT; SAPOSHNIKOVIA DIVARICATA ROOT; MORUS ALBA LEAF; ACORUS GRAMINEUS ROOT; MENTHA ARVENSIS FLOWERING TOP; CINNAMON; WATER

104 The Nose Fragrance cream

ACTIVE INGREDIENT

Menthol

Purpose

cooling Nasal discomfort relief

Uses

The product Help Inhibit The Growth of Germs In The Lesions.Help repair of nasal mucosa,Help Protecting The Nasal.Help Relieves Pollen/Dust Mites Allergy.
Help Relieves Sneezing/ Runny /Anosmia.

Do not use with other ointments, sprays or liniment. People with nasal injury is prohibited to usage. If pregnant or breast-leeding: Ask a health professional before use

Directions

clean the nasal cavity, evenly smear the product into the nasal cavity with cotton swab, gently massage to promote the absorption of the product, 2-3 times a day.

Warnings

For nasal problems only
Flammable: Keep away from excessive heat or open flame

Because the nasal cavity is inflamed for a long time,ln the early stage of use, there will be slight stimulation of heat, cool and numbness, Increased runny nose and sneezing,which is a normal performance and disappears with the reduction of symptoms.

Other Information

Store in a cool dry place with lid closed tightly

When using this product Avoid contact with the eyes. In case of contact with eyes, Stop use andrinse eyes thoroughly with water.

Keep out of reach of children: If accidentally ingested, get medical help orcontact a Poison Control Center immediately

INACTIVE INGREDIENT

Magnolia flower, Centipeda minima whole, Xanthium fruit, Angelicae Dahuricae Radix, Atractylodis macrocephalae rhizome, ARCTIUM LAPPA FRUIT, Astragali Radix, Cicadae Periostracum, Prunellae Spica Prunella vulgaris flowering, Lonicerae Flos, Schizonepetae Herba, Gleditsiae Spina, Viticis Fructus, Mulberry leaf, Mume Fructus, Acori Tatarinowii Rhizoma, Menthae Haplocalycis Herba, Saposhnikoviae Radix, Cinnamomi Cortex, PETROLATUM, Water

STOP USE

In case of contact with eyes, Stop use andrinse eyes thoroughly with water.